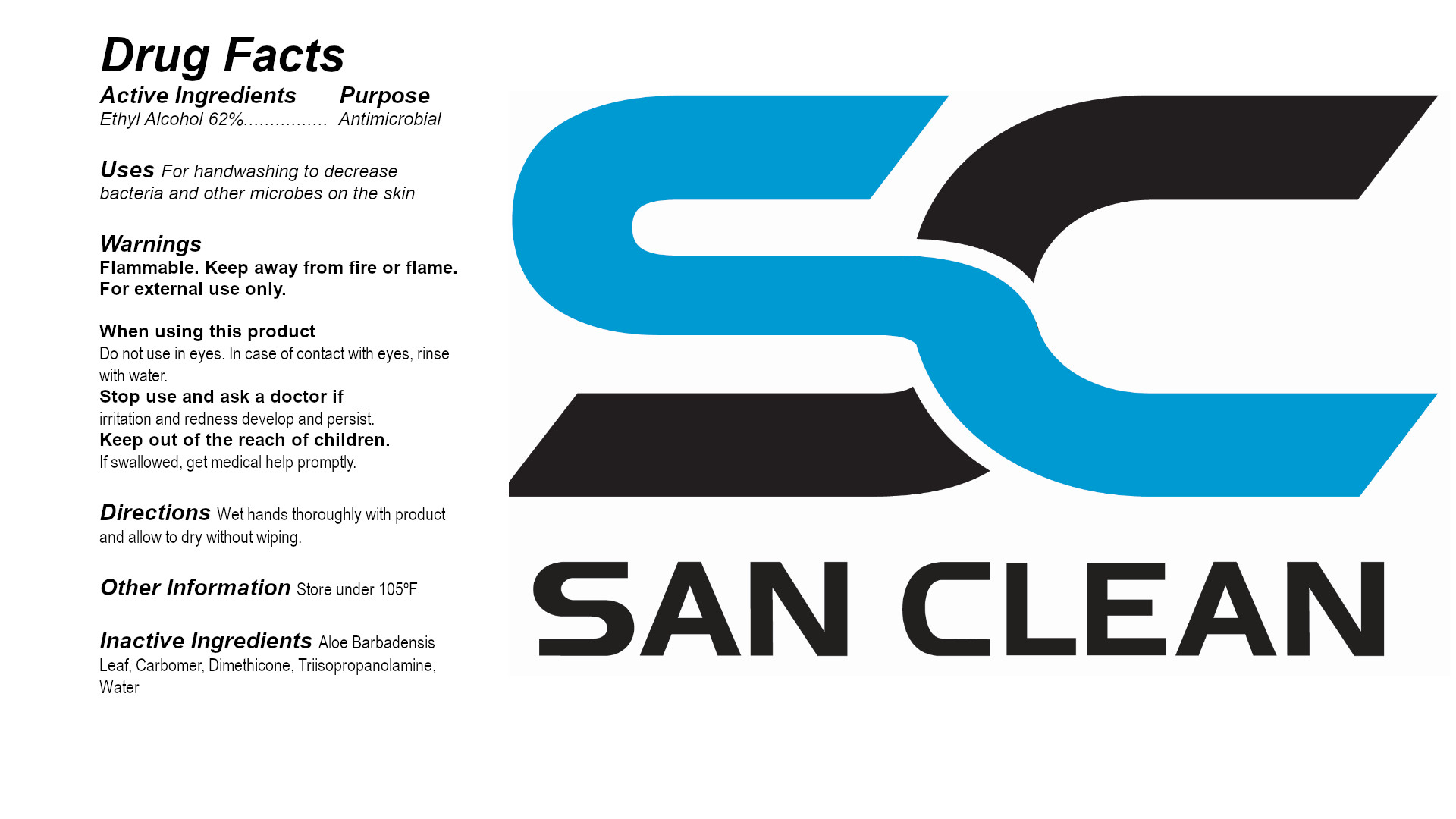 DRUG LABEL: Gel Hand Sanitizer
NDC: 75769-143 | Form: GEL
Manufacturer: Dashpost Ltd
Category: otc | Type: HUMAN OTC DRUG LABEL
Date: 20200422

ACTIVE INGREDIENTS: ALCOHOL 0.62 mL/1 mL
INACTIVE INGREDIENTS: ALOE VERA LEAF; TRIISOPROPANOLAMINE; DIMETHICONE; WATER; CARBOMER HOMOPOLYMER, UNSPECIFIED TYPE

Active Ingredients

Ethyl alcohol 62%

Purpose

Antimicrobial

Warnings

Flammable. Keep away from fire or flame. For external use only.

Do not use in eyes. In case of contact with eyes, rinse with water.

ASK DOCTOR

Stop and ask a doctor if irritation and redness develop and persist.

KEEP OUT OF REACH OF CHILDREN

Keep out of the reach of children. If swallowed, get medical help promptly.

Directions

Wet hands thoroughly with product and allow to dry without wiping.

Other Information

Store under 105ºF

Inactive Ingredients

Aloe Barbadensis Leaf, Carbomer, Dimethicone, Triisopropanolamine, Water

PACKAGE LABEL

Repackaged & Relabeled by

Dashpost Ltd

Brecksville, Ohio, 44141

www.dashpost.trade

Manufactured in U.S.A.